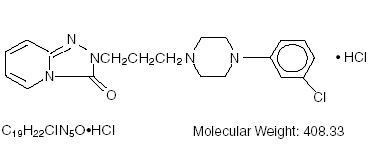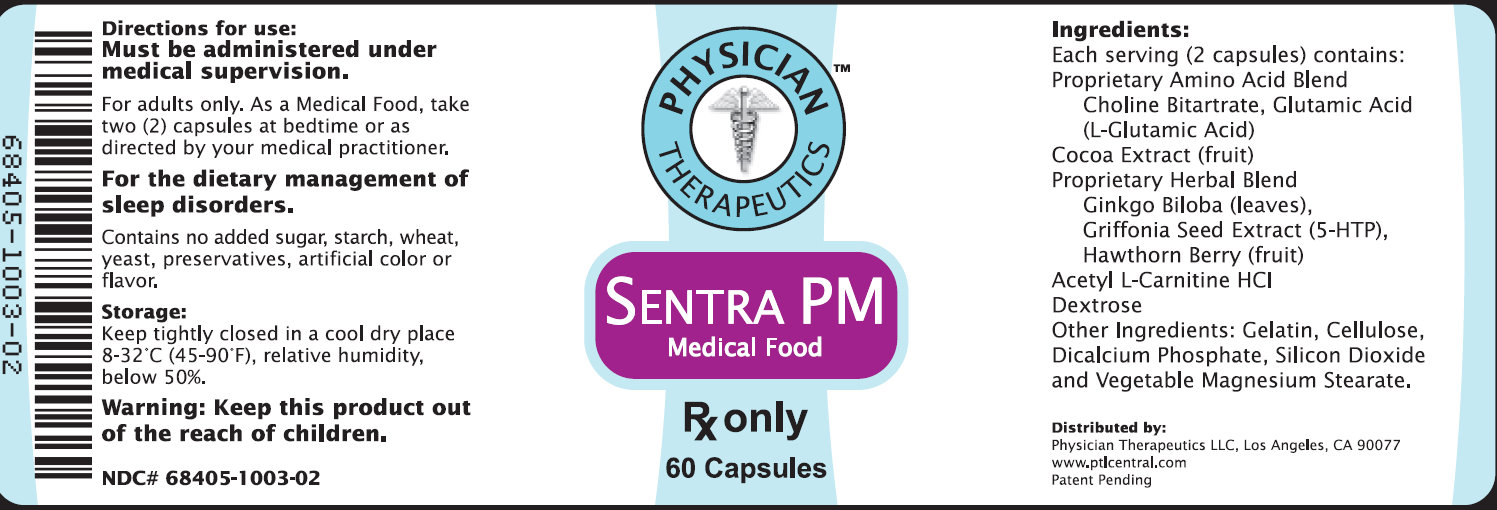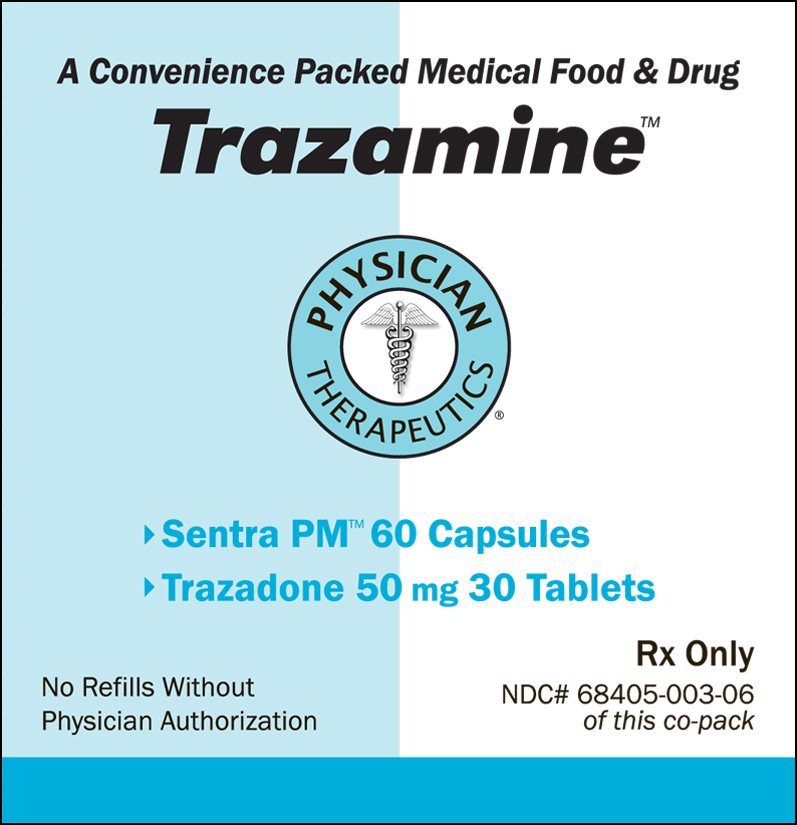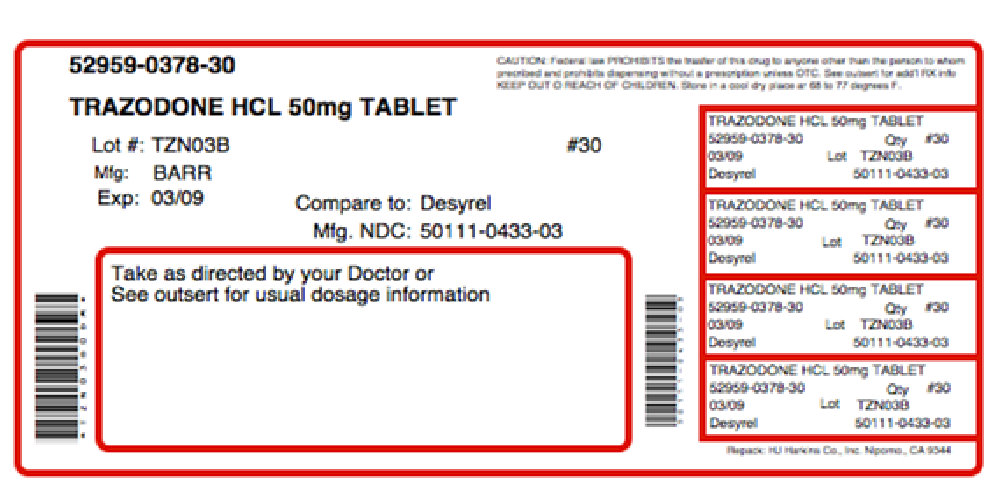 DRUG LABEL: Trazamine
                        
NDC: 68405-003 | Form: KIT | Route: ORAL
Manufacturer: Physician Therapeutics LLC
Category: prescription | Type: HUMAN PRESCRIPTION DRUG LABEL
Date: 20110801

ACTIVE INGREDIENTS: TRAZODONE HYDROCHLORIDE 50 mg/1 1; CHOLINE 250 mg/1 1
INACTIVE INGREDIENTS: SILICON DIOXIDE; ANHYDROUS LACTOSE; MAGNESIUM STEARATE; CELLULOSE, MICROCRYSTALLINE; SODIUM STARCH GLYCOLATE TYPE A POTATO; MAGNESIUM STEARATE; CELLULOSE, MICROCRYSTALLINE; MALTODEXTRIN; GELATIN

Trazamine

DESCRIPTION

Trazodone Generic Name:
Trazodone hydrochloride Dosage Form: tablet Trazodone HYDROCHLORIDE TABLETS, USP Suicidality and Antidepressant Drugs Antidepressants increased the risk compared to placebo of suicidal thinking and behavior (suicidality) in children, adolescents, and young adults in short-term studies of major depressive disorder (MDD) and other psychiatric disorders. Anyone considering the use of Trazodone HCl or any other antidepressant in a child, adolescent, or young adult must balance this risk with the clinical need. Short-term studies did not show an increase in the risk of suicidality with antidepressants compared to placebo in adults beyond age 24; there was a reduction in risk with antidepressants compared to placebo in adults aged 65 and older. Depression and certain other psychiatric disorders are themselves associated with increases in the risk of suicide.
Patients of all ages who are started on antidepressant therapy should be monitored appropriately and observed closely for clinical worsening, suicidality, or unusual changes in behavior. Families and caregivers should be advised of the need for close observation and communication with the prescriber. Trazodone HCl is not approved for use in pediatric patients. (See Warnings: Clinical Worsening and Suicide Risk, Precautions: Information for Patients, and Precautions: Pediatric Use Trazodone Description Trazodone HCl is an antidepressant chemically unrelated to tricyclic, tetracyclic, or other known antidepressant agents. Trazodone HCl is a triazolopyridine derivative designated as 2-[3-[4-(m-Chlorophenyl)-1-piperazinyl]propyl]s-triazolo[4,3-a]-pyridin-3 (2H)-one monohydrochloride. It is a white to off-white crystalline powder which is sparingly soluble in chloroform and in water. Its molecular weight is 408.3. The molecular formula is C19H22ClN5O•HCl and the structural formula is represented as follows: Each tablet, for oral administration, contains 50 mg, 100 mg or 150 mg of Trazodone hydrochloride, USP. In addition, each tablet contains the following inactive ingredients: colloidal silicon dioxide, anhydrous lactose, magnesium stearate, microcrystalline cellulose and sodium starch glycolate.

CLINICAL PHARMACOLOGY

Trazodone - Clinical Pharmacology The mechanism of Trazodone HCl’s antidepressant action in man is not fully understood. In animals, Trazodone HCl selectively inhibits its serotonin uptake by brain synaptosomes and potentiates the behavioral changes induced by the serotonin precursor, 5-hydroxytryptophan. Cardiac conduction effects of Trazodone HCl in the anesthetized dog are qualitatively dissimilar and quantitatively less pronounced than those seen with tricyclic antidepressants. Trazodone HCl is not a monoamine oxidase inhibitor and, unlike amphetamine type drugs, does not stimulate the central nervous system.

Pharmacokinetics
Absorption In humans, Trazodone is well absorbed after oral administration without selective localization in any tissue. When Trazodone is taken shortly after ingestion of food, there may be an increase in the amount of drug absorbed, a decrease in maximum concentration and a lengthening in the time to maximum concentration. Peak plasma levels occur approximately one hour after dosing when Trazodone is taken on an empty stomach or two hours after dosing when taken with food. Metabolism In vitro studies in human liver microsomes show that Trazodone is metabolized to an active metabolite, m-chlorophenylpiperazine (mCPP) by cytochrome P450 3A4 (CYP3A4).
Other metabolic pathways that may be involved in metabolism of Trazodone have not been well characterized. Elimination In some patients Trazodone may accumulate in the plasma. Drug-Drug Interactions See also PRECAUTIONS: Drug Interactions. In vitro drug metabolism studies reveal that Trazodone is a substrate of the cytochrome P450 3A4 (CYP3A4) enzyme and Trazodone metabolism can be inhibited by the CYP3A4 inhibitors ketoconazole, ritonavir, and indinavir. The effect of short-term administration of ritonavir (200 mg twice daily, 4 doses) on the pharmacokinetics of a single dose of Trazodone (50 mg) has been studied in 10 healthy subjects.
The Cmax of Trazodone increased by 34%, the AUC increased 2.4-fold, the half-life increased by 2.2-fold, and the clearance decreased by 52%. Adverse effects including nausea, hypotension, and syncope were observed when ritonavir and Trazodone were co-administered. Carbamazepine induces CYP34A. Following co-administration of carbamazepine 400 mg/day with Trazodone 100 mg to 300 mg daily, carbamazepine reduced plasma concentrations of Trazodone (as well as mCPP) by 76 and 60%, respectively, compared to pre-carbamazepine values. For those patients who responded to Trazodone HCl, one-third of the inpatients and one-half of the outpatients had a significant therapeutic response by the end of the first week of treatment. Three-fourths of all responders demonstrated a significant therapeutic effect by the end of the second week. One-fourth of responders required 2-4 weeks for a significant therapeutic response.

Indications and Usage for Trazodone
Trazodone hydrochloride tablets are indicated for the treatment of depression. The efficacy of Trazodone HCl has been demonstrated in both inpatient and outpatient settings and for depressed patients with and without prominent anxiety.
The depressive illness of patients studied corresponds to the Major Depressive Episode criteria of the American Psychiatric Association’s Diagnostic and Statistical Manual, lll.a Major Depressive Episode implies a prominent and relatively persistent (nearly every day for at least two weeks) depressed or dysphoric mood that usually interferes with daily functioning, and includes at least four of the following eight symptoms: change in appetite, change in sleep, psychomotor agitation or retardation, loss of interest in usual activities or decrease in sexual drive, increased fatigability, feelings of guilt or worthlessness, slowed thinking or impaired concentration, and suicidal ideation or attempts.

CONTRAINDICATIONS

Contraindications Trazodone hydrochloride tablets are contraindicated in patients hypersensitive to Trazodone HCl.

WARNINGS

Warnings Clinical Worsening and Suicide Risk Patients with major depressive disorder (MDD), both adult and pediatric, may experience worsening of their depression and/or the emergence of suicidal ideation and behavior (suicidality) or unusual changes in behavior, whether or not they are taking antidepressant medications, and this risk may persist until significant remission occurs.
Suicide is a known risk of depression and certain other psychiatric disorders, and these disorders themselves are the strongest predictors of suicide. There has been a longstanding concern, however, that antidepressants may have a role in inducing worsening of depression and the emergence of suicidality in certain patients during the early phases of treatment. Pooled analyses of short-term placebo-controlled trials of antidepressant drugs (SSRIs and others) showed that these drugs increase the risk of suicidal thinking and behavior (suicidality) in children, adolescents, and young adults (aged 18-24) with major depressive disorder (MDD) and other psychiatric disorders. Short-term studies did not show an increase in the risk of suicidality with antidepressants compared to placebo in adults beyond age 24; there was a reduction with antidepressants compared to placebo in adults aged 65 and older. The pooled analysis of placebo-controlled trials in children and adolescents with MDD, obsessive compulsive disorder (OCD), or other psychiatric disorders including a total of 24 short-term trials of 9 antidepressant drugs in over 4400 patients.
The pooled analyses of placebo-controlled trials in adults with MDD or other psychiatric disorders included a total of 295 short-term trials (median duration of 2 months) of 11 antidepressant drugs in over 77,000 patients. There was considerable variation in risk of suicidality among drugs, but a tendency toward an increase in the younger patients for almost all drugs studied. There were differences in absolute risk of suicidality across the different indications, with the highest incidence in MDD. The risk differences (drug vs placebo), however, were relatively stable within age strata and across indications. These risk differences (drug-placebo difference in the number of cases of suicidality per 1000 patients treated) are provided in Table 1.

Table 1
Age Range | Drug-Placebo Difference in Number of Cases of Suicidality per 1000 Patients Treated
 | Increases Compared to Placebo
Less than 18 | 14 additional cases
18-24 | 5 additional cases
 | Decreases Compared to Placebo
25-64 | 1 fewer case
Greater than or equals to 65 | 6 fewer cases

No suicides occurred in any of the pediatric trials. There were suicides in the adult trials, but the number was not sufficient to reach any conclusion about the drug effect on suicide. It is unknown whether the suicidality risk extends to longer-term use, i.e., beyond several months. However, there is substantial evidence from placebo-controlled maintenance trials in adults with depression that the use of antidepressants can delay the recurrence of depression. All patients being treated with antidepressants for any indication should be monitored appropriately and observed closely for clinical worsening, suicidality, and unusual changes in behavior, especially during the initial few months of a course of drug therapy, or at times of dose changes, either increases or decreases. The following symptoms, anxiety, agitation, panic attacks, insomnia, irritability, hostility, aggressiveness, impulsivity, akathisia (psychomotor restlessness), hypomania, and mania, have been reported in adult and pediatric patients being treated with antidepressants for major depressive disorder as well as for other indications, both psychiatric and nonpsychiatric.
Although a causal link between the emergence of such symptoms and either the worsening of depression and/or the emergence of suicidal impulses has not been established, there is concern that such symptoms may represent precursors to emerging suicidality. Consideration should be given to changing the therapeutic regimen, including possibly discontinuing the medication, in patients whose depression is persistently worse, or who are experiencing emergent suicidality or symptoms that might be precursors to worsening depression or suicidality, especially if these symptoms are severe, abrupt in onset, or were not part of the patient’s presenting symptoms. Families and caregivers of patients being treated with antidepressants for major depressive disorder or other indications, both psychiatric and nonpsychiatric, should be alerted about the need to monitor patients for the emergence of agitation, irritability, unusual changes in behavior, and the other symptoms described above, as well as the emergence of suicidality, and to report such symptoms immediately to health care providers. Such monitoring should include daily observation by families and caregivers. Prescriptions for Trazodone HCl should be written for the smallest quantity of tablets consistent with good patient management, in order to reduce the risk of overdose. Screening Patients for Bipolar Disorder A major depressive episode may be the initial presentation of bipolar disorder. It is generally believed (though not established in controlled trials) that treating such an episode with an antidepressant alone may increase the likelihood of precipitation of a mixed/manic episode in patients at risk for bipolar disorder. Whether any of the symptoms described above represent such a conversion is unknown.
However, prior to initiating treatment with an antidepressant, patients with depressive symptoms should be adequately screened to determine if they are at risk for bipolar disorder; such screening should include a detailed psychiatric history, including a family history of suicide, bipolar disorder, and depression. It should be noted that Trazodone HCl is not approved for use in treating bipolar depression. Trazodone HAS BEEN ASSOCIATED WITH THE OCCURRENCE OF PRIAPISM. IN MANY OF THE CASES REPORTED, SURGICAL INTERVENTION WAS REQUIRED AND, IN SOME OF THESE CASES, PERMANENT IMPAIRMENT OF ERECTILE FUNCTION OR IMPOTENCE RESULTED. MALE PATIENTS WITH PROLONGED OR INAPPROPRIATE ERECTIONS SHOULD IMMEDIATELY DISCONTINUE THE DRUG AND CONSULT THEIR PHYSICIAN. The detumescence of priapism and drug-induced penile erections has been accomplished by both pharmacologic, e.g., the intracavernosal injection of alpha-adrenergic stimulants such as epinephrine and norepinephrine, as well as surgical procedures.b-g Any pharmacologic or surgical procedure utilized in the treatment of priapism should be performed under the supervision of a urologist or a physician familiar with the procedure and should not be initiated without urologic consultation if the priapism has persisted for more than 24 hours.
Trazodone is not recommended for use during the initial recovery phase of myocardial infarction. Caution should be used when administering Trazodone HCl to patients with cardiac disease, and such patients should be closely monitored, since antidepressant drugs(including Trazodone HCl) have been associated with the occurrence of cardiac arrhythmias. Recent clinical studies in patients with pre-existing cardiac disease indicate that Trazodone HCl may be arrhythmogenic in some patients in that population. Arrhythmias identified include isolated PVCs, ventricular couplets, and in two patients short episodes (3-4 beats) of ventricular tachycardia.

GENERAL PRECAUTIONS

General The possibility of suicide in seriously depressed patients is inherent in the illness and may persist until significant remission occurs.
Therefore, prescriptions should be written for the smallest number of tablets consistent with good patient management. Hypotension, including orthostatic hypotension and syncope, has been reported to occur in patients receiving Trazodone HCl. Concomitant administration of antihypertensive therapy with Trazodone HCl may require a reduction in the dose of the antihypertensive drug.
Little is known about the interaction between Trazodone HCl and general anesthetics; therefore, prior to elective surgery, Trazodone HCl should be discontinued for as long as clinically feasible. As with all antidepressants, the use of Trazodone HCl should be based on the consideration of the physician that the expected benefits of therapy outweigh potential risk factors.

PATIENT COUNSELING INFORMATION

Prescribers or other health professionals should inform patients, their families, and their caregivers about the benefits and risks associated with treatment with Trazodone HCl and should counsel them in its appropriate use. A patient Medication Guide about “Antidepressant Medicines, Depression and other Serious Mental Illness, and Suicidal Thoughts or Actions” is available for Trazodone HCl.
The prescriber or health professional should instruct patients, their families, and their caregivers to read the Medication Guide and should assist them in understanding its contents. Patients should be given the opportunity to discuss the contents of the Medication Guide and to obtain answers to any questions they may have. The complete text of the Medication Guide is reprinted at the end of this document. Patients should be advised of the following issues and asked to alert their prescriber if these occur while taking Trazodone HCl. Clinical Worsening and Suicide Risk Patients, their families and their caregivers should be encouraged to be alert to the emergence of anxiety, agitation, panic attacks, insomnia, irritability, hostility, aggressiveness, impulsivity, akathisia, (psychomotor restlessness), hypomania, mania, other unusual changes in behavior, worsening of depression, and suicidal ideation, especially early during antidepressant treatment and when the dose is adjusted up or down.
Families and caregivers of patients should be advised to look for the emergence of such symptoms on a day-to-day basis, since changes may be abrupt. Such symptoms should be reported to the patient’s prescriber or health professional, especially if they are severe, abrupt in onset, or were not part of the patient’s presenting symptoms. Symptoms such as these may be associated with an increased risk for suicidal thinking and behavior and indicate a need for very close monitoring and possibly changes in the medication. Because priapism has been reported to occur in patients receiving Trazodone HCl, patients with prolonged or inappropriate penile erection should immediately discontinue the drug and consult with the physician (see WARNINGS). Antidepressants may impair the mental and/or physical abilities required for the performance of potentially hazardous tasks, such as operating an automobile or machinery; the patient should be cautioned accordingly. Trazodone HCl may enhance the response to alcohol, barbiturates, and other CNS depressants. Trazodone HCl should be given shortly after a meal or light snack. Within any individual patient, total drug absorption may be up to 20% higher when the drug is taken with food rather than on an empty stomach. The risk of dizziness/lightheadedness may increase under fasting conditions.

LABORATORY TESTS

Laboratory Tests Occasional low white blood cell and neutrophil counts have been noted in patients receiving Trazodone HCl. These were not considered clinically significant and did not necessitate discontinuation of the drug; however, the drug should be discontinued in any patient whose white blood cell count or absolute neutrophil count falls below normal levels. White blood cell and differential counts are recommended for patients who develop fever and sore throat (or other signs of infection) during therapy.

DRUG INTERACTIONS

Drug Interactions In vitro drug metabolism studies suggest that there is a potential for drug interactions when Trazodone is given with CYP3A4 inhibitors. Ritonavir, a potent CYP3A4 inhibitor, increased the Cmax, AUC, and elimination half-life, and decreased clearance of Trazodone after administration of ritonavir twice daily for 2 days. Adverse effects including nausea, hypotension, and syncope were observed when ritonavir and Trazodone were co-administered. It is likely that ketoconazole, indinavir, and other CYP3A4 inhibitors such as intraconazole or nefazadone may lead to substantial increases in Trazodone plasma concentrations, with the potential for adverse effects.
If Trazodone is used with a potent CYP3A4 inhibitor, a lower dose of Trazodone should be considered. Carbamazepine reduced plasma concentrations of Trazodone when co-administered. Patients should be more closely monitored to see if there is a need for an increased dose of Trazodone when taking both drugs. Increased serum digoxin or phenytoin levels have been reported to occur in patients receiving Trazodone concurrently with either of those two drugs. It is not known whether interactions will occur between monoamine oxidase (MAO) inhibitors and Trazodone HCl.
Due to the absence of clinical experience, if MAO inhibitors are discontinued shortly before or are to be given concomitantly with Trazodone HCl, therapy should be initiated cautiously with gradual increase in dosage until optimum response is achieved. Therapeutic Interactions Concurrent administration with electroshock therapy should be avoided because of the absence of experience in this area. There have been reports of increased and decreased prothrombin time occurring in patients taking warfarin and Trazodone HCl.

CARCINOGENESIS AND MUTAGENESIS AND IMPAIRMENT OF FERTILITY

Carcinogenesis, Mutagenesis, Impairment of Fertility No drug- or dose-related occurrence of carcinogenesis was evident in rats receiving Trazodone HCl in daily oral doses up to 300 mg/kg for 18 months.

PREGNANCY

Pregnancy Teratogenic Effects: Pregnancy Category C Trazodone hydrochloride has been shown to cause increased fetal resorption and other adverse effects on the fetus in two studies using the rat when given at dose levels approximately 30-50 times the proposed maximum human dose.
There was also an increase in congenital anomalies in one of three rabbit studies at approximately 15-50 times the maximum human dose. There are no adequate and well-controlled studies in pregnant women. Trazodone HCl should be used during pregnancy only if the potential benefit justifies the potential risk to the fetus.

NURSING MOTHERS

Nursing Mothers Trazodone HCl and/or its metabolites have been found in the milk of lactating rats, suggesting that the drug may be secreted in human milk. Caution should be exercised when Trazodone HCl is administered to a nursing woman.

PEDIATRIC USE

Pediatric Use Safety and effectiveness in the pediatric population have not been established (see BOX WARNING and WARNINGS—Clinical Worsening and Suicide Risk). Anyone considering the use of Trazodone HCl in a child or adolescent must balance the potential risks with the clinical need.

ADVERSE REACTIONS

Adverse Reactions Because the frequency of adverse drug effects is affected by diverse factors (e.g., drug dose, method of detection, physician judgment, disease under treatment, etc.) a single meaningful estimate of adverse event incidence is difficult to obtain. This problem is illustrated by the variation in adverse event incidence observed and reported from the inpatients and outpatients treated with Trazodone HCl.

It is impossible to determine precisely what accounts for the differences observed Clinical Trial Reports Table 2 below is presented solely to indicate the relative frequency of adverse events reported in representative controlled clinical studies conducted to evaluate the safety and efficacy of Trazodone HCl. The figures cited cannot be used to predict precisely the incidence of untoward events in the course of usual medical practice where patient characteristics and other factors often differ from those which prevailed in clinical trials. These incidence figures, also, cannot be compared with those obtained from other clinical studies involving related drug products and placebo as each group of drug trials is conducted under a different set of conditions. Table 2 Treatment Emergent Symptom Incidence InpatientsOutpatients T1 P2 T3 P4 Number of Patients 142 95 157 158 % of Patients Reporting Allergic Skin Condition/Edema 2.8 1.1 7.0 1.3 Autonomic Blurred Vision 6.3 4.2 14.7 3.8 Constipation 7.0 4.2 7.6 5.7 Dry Mouth 14.8 8.4 33.8 20.3 Cardiovascular Hypertension 2.1 1.1 1.3 *5 Hypotension 7.0 1.1 3.8 0.0 Shortness of Breath *6 1.1 1.3 0.0 Syncope 2.8 2.1 4.5 1.3 Tachycardia/Palpitations 0.0 0.0 7.0 7.0 CNS Anger/Hostility 3.5 6.3 1.3 2.5 Confusion 4.9 0.0 5.7 7.6 Decreased Concentration 2.8 2.1 1.3 0.0 Disorientation 2.1 0.0 *7 0.0 Dizziness/Lightheadedness 19.7 5.3 28.0 15.2 Drowsiness 23.9 6.3 40.8 19.6 Excitement 1.4 1.1 5.1 5.7 Fatigue 11.3 4.2 5.7 2.5 Headache 9.9 5.3 19.8 15.8 Insomnia 9.9 10.5 6.4 12.0 Impaired Memory 1.4 0.0 *8 *9 Nervousness 14.8 10.5 6.4 8.2 Gastrointestinal Abdominal/Gastric Disorder Bad Taste in Mouth 1.4 0.0 0.0 0.0 Diarrhea 0.0 1.1 4.5 1.9 Nausea/Vomiting 9.9 1.1 12.7 9.5 Musculoskeletal Musculoskeletal Aches/Pains 5.6 3.2 5.1 2.5 Neurological Incoordination 4.9 0.0 1.9 0.0 Paresthesia 1.4 0.0 0.0 *10 Tremors 2.8 1.1 5.1 3.8 Sexual Function Decreased Libido *11 1.1 1.3 *12 Other Decreased Appetite 3.5 5.3 0.0 *13 Eyes Red/Tired/Itching 2.8 0.0 0.0 0.0 Head Full-Heavy 2.8 0.0 0.0 0.0 Malaise 2.8 0.0 0.0 0.0 Nasal/Sinus Congestion 2.8 0.0 5.7 3.2 Nightmares/Vivid Dreams *14 1.1 5.1 5.7 Sweating/Clamminess 1.4 1.1 *15 *16 Tinnitus 1.4 0.0 0.0 *17 Weight Gain 1.4 0.0 4.5 1.9 Weight Loss *18 3.2 5.7 2.5 1 T=Trazodone HCl 2 P=Placebo 3 4 5 Incidence less than 1% 6 7 8 9 10 11 12 13 14 15 16 17 18 Occasional sinus bradycardia has occurred in long-term studies.

In addition to the relatively common (i.e., greater than 1%) untoward events enumerated above, the following adverse events have been reported to occur in association with the use of Trazodone HCl in the controlled clinical studies: akathisia, allergic reaction, anemia, chest pain, delayed urine flow, early menses, flatulence, hallucinations/delusions, hematuria, hypersalivation, hypomania, impaired speech, impotence, increased appetite, increased libido, increased urinary frequency, missed periods, muscle twitches, numbness, and retrograde ejaculation. Post Introduction Reports: Although the following adverse reactions have been reported in Trazodone HCl users, the causal association has neither been confirmed nor refuted. Voluntary reports received since market introduction include the following: abnormal dreams, agitation, alopecia, anxiety, aphasia, apnea, ataxia, breast enlargement or engorgement, cardiospasm, cerebrovascular accident, chills, cholestatis, clitorism, congestive heart failure, diplopia, edema, extrapyramidal symptoms, grand mal seizures, hallucinations, hemolytic anemia, hirsutism, hyperbilirubinemia, increased amylase, increased salivation, insomnia, leukocytosis, leukonychia, jaundice, lactation, liver enzyme alterations, methemoglobinemia, nausea/vomiting (most frequently), paresthesia, paranoid reaction, priapism (see WARNINGS and PRECAUTIONS, Information for Patients; some patients have required surgical intervention), pruritus, psoriasis, psychosis, rash, stupor, inappropriate ADH syndrome, tardive dyskinesia, unexplained death, urinary incontinence, urinary retention, urticaria, vasodilation, vertigo, and weakness. Cardiovascular system effects which have been reported include the following: conduction block orthostatic hypotension and syncope, palpitations, bradycardia, atrial fibrillation, myocardial infarction, cardiac arrest, arrhythmia, and ventricular ectopic activity, including ventricular tachycardia (see WARNINGS).

OVERDOSAGE

Overdosage Animal Oral LD50: The oral LD50 of the drug is 610 mg/kg in mice, 486 mg/kg in rats, and 560 mg/kg in rabbits. Signs and Symptoms: Death from overdose has occurred in patients ingesting Trazodone HCl and other drugs concurrently (namely, alcohol; alcohol + chloral hydrate + diazepam; amobarbital; chlordiazepoxide; or meprobamate).

The most severe reactions reported to have occurred with overdose of Trazodone HCl alone have been priapism, respiratory arrest, seizures, and EKG changes. The reactions reported most frequently have been drowsiness and vomiting. Overdosage may cause an increase in incidence or severity of any of the reported adverse reactions (see ADVERSE REACTIONS). Treatment There is no specific antidote for Trazodone HCl. Treatment should be symptomatic and supportive in the case of hypotension or excessive sedation. Any patient suspected of having taken an overdose should have the stomach emptied by gastric lavage. Forced diuresis may be useful in facilitating elimination of the drug.

Trazodone Dosage and Administration

The dosage should be initiated at a low level and increased gradually, noting the clinical response and any evidence of intolerance. Occurrence of drowsiness may require the administration of a major portion of the daily dose at bedtime or a reduction of dosage. Trazodone HCl should be taken shortly after a meal or light snack. Symptomatic relief may be seen during the first week with optimal antidepressant effects typically evident within two weeks. Twenty-five percent of those who respond to Trazodone HCl require more than two weeks (up to four weeks) of drug administration.

Usual Adult Dosage: An initial dose of 150 mg/day in divided doses is suggested. The dose may be increased by 50 mg/day every three to four days. The maximum dose for outpatients usually should not exceed 400 mg/day in divided doses. Inpatients (i.e., more severely depressed patients) may be given up to but not in excess of 600 mg/day in divided doses. Maintenance: Dosage during prolonged maintenance therapy should be kept at the lowest effective level. Once an adequate response has been achieved, dosage may be gradually reduced, with subsequent adjustment depending on therapeutic response. Although there has been no systematic evaluation of the efficacy of Trazodone beyond 6 weeks, it is generally recommended that a course of antidepressant drug treatment should be continued for several months.

HOW SUPPLIED

How is Trazodone Supplied Trazodone Hydrochloride Tablets, USP: 50 mg - White, round, scored tablets in blisters of 30 Debossed: PLIVA 433 100 mg - White, round, scored tablets in blisters of 30 Debossed: PLIVA 434 Dispense in a tight, light-resistant container. Store at 20° to 25°C (68° to 77°F) [See USP Controlled Room Temperature]. Repackaged by: Contract Pharmacy Services-PA 125 Titus Ave Suite 200 Warrington, PA 18976 USA Original--02/2010--NJW

REFERENCES

REFERENCES (a) Williams JBW, Ed: Diagnostic and Statistical Manual of Mental Disorders lll, American Psychiatric Association, May, 1980. (b) Lue TF, Physiology of erection and pathophysiology of impotence. In: Wash PC, Retik AB, Stamey TA, Vaughan ED, eds. Campbell’s Urology. Sixth edition. Philadelphia: W.B. Saunders: 1992: 722-725. (c) Goldstein I, Krane RJ, Diagnosis and therapy of erectile dysfunction. In: Wash PC. Retik AB, Stamey TA, Vaughan ED, eds. Campbell’s Urology. Sixth edition. Philadelphia: W.B. Saunders: 1992: 3071-3072. (d) Yealy DM, Hogya PT: Priapism. Emerg Med Clin North Am, 1988: 6:509-520. (e) Banos JE, Bosch F, Farre M. Drug-induced priapism, its aetiology, incidence and treatment. Med Toxicol Adverse Drug Exp. 1989: 4:46-58. (f) O’Brien WM, O’Connor KP, Lynch JH. Priapism: current concepts. Ann Emerg Med. 1989: 980-983. (g) Bardin ED, Krieger JN. Pharmacological priapism: comparison of Trazodone- and papaverine-associated cases. Int Urol Nephrol. 1990: 22:147- 152.

MEDICATION GUIDE

Medication Guide Antidepressant Medicines, Depression and other Serious Mental Illnesses, and Suicidal Thoughts or Actions Read the Medication Guide that comes with you or your family member’s antidepressant medicine.

This Medication Guide is only about the risk of suicidal thoughts and actions with antidepressant medicines.

Talk to your, or your family member’s, healthcare provider about: • all risks and benefits of treatment with antidepressant medicines • all treatment choices for depression or other serious mental illness What is the most important information I should know about antidepressant medicines, depression and other serious mental illnesses, and suicidal thoughts or actions?

1. Antidepressant medicines may increase suicidal thoughts or actions in some children, teenagers, and young adults within the first few months of treatment.

2. Depression and other serious mental illnesses are the most important causes of suicidal thoughts and actions. Some people may have a particularly high risk of having suicidal thoughts or actions. These include people who have (or have a family history of) bipolar illness (also called manic-depressive illness) or suicidal thoughts or actions.

3. How can I watch for and try to prevent suicidal thoughts and actions in myself or a family member? • Pay close attention to any changes, especially sudden changes, in mood, behaviors, thoughts, or feelings. This is very important when an antidepressant medicine is started or when the dose is changed. • Call the healthcare provider right away to report new or sudden changes in mood, behavior, thoughts, or feelings. • Keep all follow-up visits with the healthcare provider as scheduled. Call the healthcare provider between visits as needed, especially if you have concerns about symptoms. Call a healthcare provider right away if you or your family member has any of the following symptoms, especially if they are new, worse, or worry you:

• thoughts about suicide or dying

• new or worse irritability

• attempts to commit suicide

• acting aggressive, being angry, or violent

• new or worse depression

• acting on dangerous impulses

• new or worse anxiety

• an extreme increase in activity and talking (mania)

• feeling very agitated or restless

• other unusual changes in behavior or mood

• panic attacks

• trouble sleeping (insomnia)

What else do I need to know about antidepressant medicines? • Never stop an antidepressant medicine without first talking to a healthcare provider. Stopping an antidepressant medicine suddenly can cause other symptoms. • Antidepressants are medicines used to treat depression and other illnesses. It is important to discuss all the risks of treating depression and also the risks of not treating it. Patients and their families or other caregivers should discuss all treatment choices with the healthcare provider, not just the use of antidepressants. • Antidepressant medicines have other side effects. Talk to the healthcare provider about the side effects of the medicine prescribed for you or your family member. • Antidepressant medicines can interact with other medicines. Know all of the medicines that you or your family member takes. Keep a list of all medicines to show the healthcare provider. Do not start new medicines without first checking with your healthcare provider. • Not all antidepressant medicines prescribed for children are FDA approved for use in children. Talk to your child’s healthcare provider for more information. Call your doctor for medical advice about side effects. You may report side effects to FDA at 1-800-FDA-1088. This Medication Guide has been approved by the U.S. Food and Drug Administration for all antidepressants. Mfg by PLIVA® Hrvatska d.o.o., Zagreb Croatia for PLIVA®, Inc. Pomona, NY 10970 Dist. by Barr Laboratories, Inc., Pomona, NY 10970 Revised January 2008 BR-433, 434, 441 Z21-0433 c/n.1 FLEXIDOSE® is a registered trademark of PLIVA®, Inc. for its tablets. The trapezoidal shaped tablet is a trademark and original design of PLIVA® Inc. Repackaged by: Contract Pharmacy Services-PA 125 Titus Ave Suite 200 Warrington, PA 18976 USA Original--02/2010--NJW

PACKAGE LABEL

Packaged by Bryant Ranch North Hollywood CA 91605 Trazadone 50mg Tablet Compare To Desyrel 50mg Tablet Barr Laboratories NC #30 EXP 02/09 NDC 6362915132 May cause dizziness or drowsiness Keep all drugs out of reach of children

LOT 14507

Rx Only

PACKAGE LABEL

A convenience Packed Medical Food and Drug Trazamine PHYSICIAN THERAPEUTICS Sentra PM 60 Capsules Trazadone 50mg 30 Tablets No Refills Without Physician Authorization Rx Only NDC # 68405-8003-06 of this co-pack For the Dietary Management of Sleep Disorders. Two capsules at bedtime or as directed by physician. See product label and insert Sentra PM Medical Food As prescribed by physician. See product label and product information insert. Trazadone 50mg Rx Drug

Sentra PM™PRODUCT INFORMATION

Sentra PM (U.S. patent pending) capsules by oral administration. A specially formulated Medical Food product, consisting of a proprietary blend of amino acids and polyphenol ingredients in specific proportions, for the dietary management of the metabolic processes of sleep disorders (SD). Must be administered under physician supervision.

Medical Foods Medical Food products are often used in hospitals (e.g., for burn victims or kidney dialysis patients) and outside of a hospital setting under a physician’s care for the dietary management of diseases in patients with particular medical or metabolic needs due to their disease or condition. Congress defined "Medical Food" in the Orphan Drug Act and Amendments of 1988 as "a system which is formulated to be consumed or administered enterally [or orally] under the supervision of a physician and which is intended for the specific dietary management of a disease or condition for which distinctive nutritional requirements, based on recognized scientific principles, are established by medical evaluation." Medical Foods are complex formulated products, requiring sophisticated and exacting technology. Sentra PM has been developed, manufactured, and labeled in accordance with both the statutory and the FDA regulatory definition of a Medical Food. Sentra PM must be used while the patient is under the ongoing care of a physician.

SLEEP DISORDERS (SD)
SD as a Metabolic Deficiency Disease A critical component of the definition of a Medical Food is the requirement for a distinctive nutritional deficiency. FDA scientists have proposed a physiologic definition of a distinctive nutritional deficiency as follows: “the dietary management of patients with specific diseases requires, in some instances, the ability to meet nutritional requirements that differ substantially from the needs of healthy persons. For example, in establishing the recommended dietary allowances for general, healthy population, the Food and Nutrition Board of the Institute of Medicine National Academy of Sciences, recognized that different or distinctive physiologic requirements may exist for certain persons with "special nutritional needs arising from metabolic disorders, chronic diseases, injuries, premature birth, other medical conditions and drug therapies. Thus, the distinctive nutritional needs associated with a disease reflect the total amount needed by a healthy person to support life or maintain homeostasis, adjusted for the distinctive changes in the nutritional needs of the patient as a result of the effects of the disease process on absorption, metabolism, and excretion.” It was also proposed that in patients with certain disease states who respond to nutritional therapies, a physiologic deficiency of the nutrient is assumed to exist. For example, if a patient with sleep disorders responds to a tryptophan formulation by improving the duration and quality of sleep, a deficiency of tryptophan is assumed to exist.

Patients with sleep disorders are known to have nutritional deficiencies of tryptophan, choline, flavonoids, and certain antioxidants. Patients with sleep disorders frequently exhibit reduced plasma levels of tryptophan and have been shown to respond to oral administration of tryptophan or a 5-hydoxytryptophan formulation. Research has shown that tryptophan reduced diets result in a fall of circulating tryptophan. Patients with sleep disorders have activation of the tryptophan degradation pathway that increases the turnover of tryptophan leading to a reduced level of production of serotonin for a given tryptophan blood level. Research has also shown that a genetic predisposition can lead to increased tryptophan requirements in certain patients with sleep disorders.

Choline is required to fully potentiate acetylcholine synthesis by brain neurons. A deficiency of choline leads to reduced acetylcholine production by the neurons. Low fat diets, frequently used by patients with sleep disorders, are usually choline deficient. Flavonoids potentiate the production of acetylcholine by the neurons thereby inducing REM sleep. Low fat diets and diets deficient in flavonoid rich foods result in inadequate flavonoid concentrations, impeding acetylcholine production in certain patients with sleep disorders. Provision of tryptophan, choline, and flavonoids with antioxidants, in specific proportions can restore the production of beneficial serotonin and acetylcholine, thereby improving sleep quality.

PRODUCT DESCRIPTION

Primary Ingredients
Sentra PM consists of a proprietary blend of amino acids, cocoa, ginkgo biloba and flavonoids in specific proportions. These ingredients fall into the category of “Generally Regarded as Safe” (GRAS) as defined by the Food and Drug Administration (FDA) (Sections 201(s) and 409 of the Federal Food, Drug, and Cosmetic Act). A GRAS substance is distinguished from a food additive on the basis of the common knowledge about the safety of the substance for its intended use. The standard for an ingredient to achieve GRAS status requires not only technical demonstration of non-toxicity and safety, but also general recognition of safety through widespread usage and agreement of that safety by experts in the field. Many ingredients have been determined by the U.S. Food and Drug Administration (FDA) to be GRAS, and are listed as such by regulation, in Volume 21 Code of Federal Regulations (CFR) Sections 182, 184, and 186.

Amino Acids
Amino Acids are the building blocks of protein. All amino acids are GRAS listed as they have been ingested by humans for thousands of years. The doses of the amino acids in Sentra PM are equivalent to those found in the usual human diet; however the formulation uses specific ratios of the key ingredients to elicit a therapeutic response. Patients with sleep disorders may require an increased amount of certain amino acids that cannot be obtained from normal diet alone. Tryptophan, for example, is an obligatory amino acid. The body cannot make tryptophan and must obtain tryptophan from the diet. Tryptophan is needed to produce serotonin. Serotonin is required to induce sleep. Patients with sleep disorders have altered serotonin metabolism. Some patients with sleep disorders have a resistance to the use of tryptophan that is similar to the mechanism found in insulin resistance that is genetically determined. Patients with sleep disorders frequently cannot acquire sufficient tryptophan from the diet without ingesting a prohibitively large amount of calories, particularly protein rich calories.

Flavonoids
Flavonoids are a group of phytochemical compounds found in all vascular plants including fruits and vegetables. They are a part of a larger class of compounds known as polyphenols. Many of the therapeutic or health benefits of colored fruits and vegetables, cocoa, red wine, and green tea are directly related to their flavonoid content. The specially formulated flavonoids found in Sentra PM cannot be obtained from conventional foods in the necessary proportions to elicit a therapeutic response.

Other Ingredients
Sentra PM contains the following inactive or other ingredients, as fillers, excipients, and colorings: magnesium stearate, microcrystalline cellulose, Maltodextrin NF, gelatin (as the capsule material).

Physical Description
Sentra PM is a yellow to light brown powder. Sentra PM contains L-Glutamic Acid, 5-Hydroxytryptophan as Griffonia Seed Extract, Acetylcarnitine HCL, Choline Bitartrate, Cinnamon, Cocoa, Ginkgo Biloba, and Hawthorn Berry.

CLINICAL PHARMACOLOGY

Mechanism of Action
Sentra PM acts by restoring and maintaining the balance of the neurotransmitters, serotonin and acetylcholine, that are associated with sleep disorders.

Metabolism
The amino acids in Sentra PM are primarily absorbed by the stomach and small intestines. All cells metabolize the amino acids in Sentra PM. Circulating tryptophan and choline blood levels determine the production of serotonin and acetylcholine.

Excretion
Sentra PM is not an inhibitor of cytochrome P450 1A2, 2C9, 2C19, 2D6, or 3A4. These isoenzymes are principally responsible for 95% of all detoxification of drugs, with CYP3A4 being responsible for detoxification of roughly 50% of drugs. Amino acids do not appear to have an effect on drug metabolizing enzymes.

INDICATIONS FOR USE
Sentra PM is intended for the clinical dietary management of the metabolic processes associated with sleep disorders.

CLINICAL EXPERIENCE
The administration of Sentra PM has demonstrated significant functional improvement in the quality and quantity of sleep when used for the dietary management of the metabolic processes associated with sleep disorders. Administration of Sentra PM results in the induction and maintenance of sleep in patients with sleep disorders. Sentra PM has no effect on normal blood pressure.

PRECAUTIONS AND CONTRAINDICATIONS
Sentra PM is contraindicated in an extremely small number of patients with hypersensitivity to any of the nutritional components of Sentra PM.

ADVERSE REACTIONS
Oral supplementation with L-tryptophan or choline at high doses up to 15 grams daily is generally well tolerated. The most common adverse reactions of higher doses — from 15 to 30 grams daily — are nausea, abdominal cramps, and diarrhea. Some patients may experience these symptoms at lower doses. The total combined amount of amino acids in each Sentra PM capsule does not exceed 400 mg.

DRUG INTERACTIONS
Sentra PM does not directly influence the pharmacokinetics of prescription drugs. Clinical experience has shown that administration of Sentra PM may allow for lowering the dose of co-administered drugs under physician supervision.

OVERDOSAGE

OVERDOSE
There is a negligible risk of overdose with Sentra PM as the total dosage of amino acids in a one month supply (60 capsules) is less than 24 grams. Overdose symptoms may include diarrhea, weakness, and nausea.

POST-MARKETING SURVEILLANCE
Post-marketing surveillance has shown no serious adverse reactions. Reported cases of mild rash and itching may have been associated with allergies to Sentra PM flavonoid ingredients, including cinnamon, cocoa, and chocolate. The reactions were transient in nature and subsided within 24 hours.

DOSAGE AND ADMINISTRATION
Recommended Administration For the dietary management of the metabolic processes associated with sleep disorders. Take (2) capsules daily at bedtime. An additional dose of one or two capsules may be taken after awakenings during the night. As with most amino acid formulations Sentra PM should be taken without food to increase the absorption of key ingredients.

How Supplied
Sentra PM is supplied in red and white, size 0 capsules in bottles of 60 capsules.

Physician Supervision
Sentra PM is a Medical Food product available by prescription only and must be used while the patient is under ongoing physician supervision.

Sentra PM is supplied to physicians in a recyclable plastic bottle with a child-resistant cap.

U.S. patents pending.

Manufactured by Arizona Nutritional Supplements, Inc. Chandler AZ 85225

Distributed by Physician Therapeutics LLC, Los Angeles, CA 90077. www.ptlcentral.com

© Copyright 2003-2006, Physician Therapeutics LLC, all rights reserved

NDC # 68405-1003-02

Storage
Store at room temperature, 59-86OF (15-30OC). Protect from light and moisture.

PACKAGE LABEL

PHYSICIAN THERAPEUTICS

SENTRA PM
Medical Food

Rx only

60 Capsules

Directions for use:
Must be administered under medical supervision.

For adults only. As a Medical Food, take two (2) capsules at bedtime or as directed by your medical practitioner.

For the dietary management of sleep disorders.

Contains no added sugar, starch, wheat, yeast, preservatives, artificial color or flavor.

Storage:
Keep tightly closed in a cool dry place 8-32^0 C (45-90^0F), relative humidity, below 50%.

Warning: Keep this product out of the reach of children.

NDC# 68405-1003-02

Ingredients:
Each serving (2 capsules) contains:

Proprietary Amino Acid blend Choline Bitartrate, Glutamic Acid (L-Glutamic Acid), Cocoa Extract (fruit), Proprietary Herbal Blend Ginkgo Biloba (leaves), Griffonia Seed Extract (5-HTP), Hawthorn Berry (fruit), Acetyl L-Carnitine HCl, Dextrose

Other Ingredients: Gelatin, Cellulose, Dicalcium Phosphate, Silicon Dioxide and Vegetable Magnesium Stearate.

Distributed by:
Physician Therapeutics LLC, Los Angeles, CA 90077
www.ptlcentral.com
Patent Pending